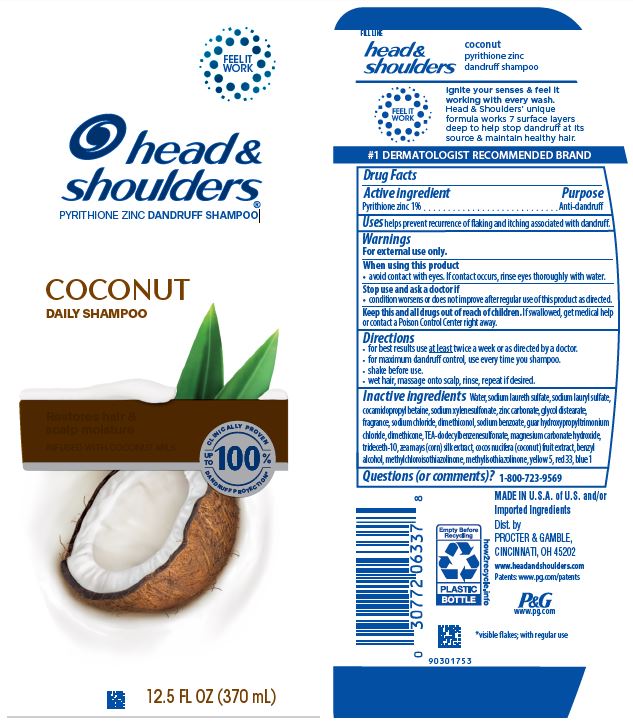 DRUG LABEL: Head and Shoulders Coconut Daily
NDC: 69423-315 | Form: SHAMPOO
Manufacturer: The Procter & Gamble Manufacturing Company
Category: otc | Type: HUMAN OTC DRUG LABEL
Date: 20251216

ACTIVE INGREDIENTS: PYRITHIONE ZINC 1 g/100 mL
INACTIVE INGREDIENTS: METHYLCHLOROISOTHIAZOLINONE; CORN SILK; D&C RED NO. 33; FD&C YELLOW NO. 5; FD&C BLUE NO. 1; COCONUT; GUAR HYDROXYPROPYLTRIMONIUM CHLORIDE (1.7 SUBSTITUENTS PER SACCHARIDE); WATER; SODIUM LAURETH-3 SULFATE; DIMETHICONE; ZINC CARBONATE; GLYCOL DISTEARATE; SODIUM XYLENESULFONATE; COCAMIDOPROPYL BETAINE; SODIUM CHLORIDE; SODIUM BENZOATE; MAGNESIUM CARBONATE HYDROXIDE; SODIUM LAURYL SULFATE; DIMETHICONOL GUM; TRIETHANOLAMINE DODECYLBENZENESULFONATE; TRIDECETH-10; METHYLISOTHIAZOLINONE; BENZYL ALCOHOL

Head and Shoulders® Coconut Daily Shampoo

Drug Facts

Active ingredient

Pyrithione zinc 1%

Purpose

Anti-dandruff

Uses

helps prevent recurrence of flaking and itching associated with dandruff.

Warnings

For external use only.

When using this product

- avoid contact with eyes. If contact occurs, rinse eyes thoroughly with water.

Stop use and ask a doctor if

- condition worsens or does not improve after regular use of this product as directed.

KEEP OUT OF REACH OF CHILDREN

Keep this and all drugs out of reach of children. If swallowed, get medical help or contact a Poison Control Center right away.

Directions

- for best results use at least twice a week or as directed by a doctor.
- for maximum dandruff control, use every time you shampoo.
- shake before use.
- wet hair, massage onto scalp, rinse, repeat if desired.

Inactive ingredients

Water, sodium laureth sulfate, sodium lauryl sulfate, cocamidopropyl betaine, sodium xylenesulfonate, zinc carbonate, glycol distearate, fragrance, sodium chloride, dimethiconol, sodium benzoate, guar hydroxypropyltrimonium chloride, dimethicone, TEA-dodecylbenzenesulfonate, magnesium carbonate hydroxide, trideceth-10, zea mays (corn) silk extract, cocos nucifera (coconut) fruit extract, benzyl alcohol,methylchloroisothiazolinone,methylisothiazolinone, yellow 5, red 33, blue 1

Questions (or comments)?

1-800-723-9569

Dist. by PROCTER & GAMBLE,
CINCINNATI, OH 45202

PRINCIPAL DISPLAY PANEL - 370 mL Bottle Label

head &
shoulders ®

pyrithione zinc dandruff shampoo

COCONUT

DAILY SHAMPOO

RESTORES HAIR & SCALP MOISTURE

INFUSED WITH COCONUT MILK

12.5 FL OZ (370 mL)